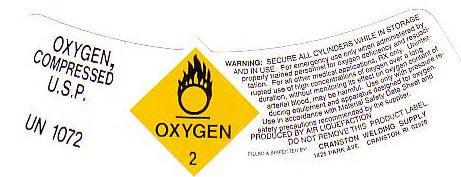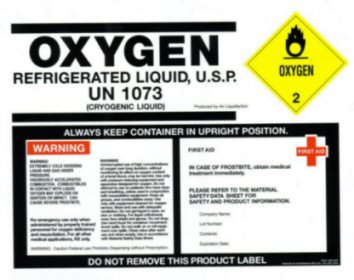 DRUG LABEL: OXYGEN
NDC: 23021-001 | Form: GAS
Manufacturer: Cranston Welding Supply Company
Category: prescription | Type: HUMAN PRESCRIPTION DRUG LABEL
Date: 20100101

ACTIVE INGREDIENTS: OXYGEN 99 L/100 L

OXYGEN COMPRESSED LABEL

OXYGEN COMPRESSED U.S.P. UN 1072 OXYGEN-2

WARNING: SECURE ALL CYLINDERS WHILE IN STORAGE AND IN USE. FOR EMERGENCY USE ONLY WHEN ADMINISTERED BY PROPERLY TRAINED PERSONNEL FOR OXYGEN DEFICIENCY AND RESUSCITATION. FOR ALL OTHER MEDICAL APPLICATIONS Rx ONLY. USE ONLY WITH PRESSURE REDUCING EQUIPMENT AND APPARATUS DESIGNED FOR OXYGEN. USE IN ACCORDANCE WITH MATERIAL SAFETY DATA SHEET AND SAFETY PRECAUTIONS RECOMMENDED BY SUPPLIER. PRODUCED BY AIR LIQUEFACTION.

PRODUCT WARNINGS AND PRECAUTIONS

WARNING! UNINTERRUPTED USE OF HIGH CONCENTRATIONS OF OXYGEN OVER LONG DURATIONS WITHOUT MONITORING ITS EFFECT ON OXYGEN CONTENT OF ARTERIAL BLOOD MAY BE HARMFUL.

DO NOT REMOVE THIS PRODUCT LABEL.

REFRIGERATED LIQUID LABEL

OXYGEN REFRIGERATED LIQUID, U.S.P.
UN 1073 (CRYOGENIC LIQUID)
Produced by Air Liquefaction
OXYGEN 2
ALWAYS KEEP CONTAINER IN UPRIGHT POSITION
For
emergency use only when administered by properly trained personnel for
oxygen deficiency and resuscitation. For all other medical applications
RX only. Warning: Caution Federal Law Prohibits Dispensing without
Prescription. First Aid IN CASE OF FROSTBITE, obtain medical treatment
immediately.
PLEASE REFER TO THE MATERIAL SAFETY DATA SHEET FOR SAFETY AND PRODUCT INFORMATION.
WARNING! EXTREMELY COLD OXIDIZING LIQUID AND GAS UNDER PRESSURE. VIGOROUSLY ACCELERATES COMBUSTION.
COMBUSTIBLES IN CONTACT WITH LIQUID OXYGEN MAY EXPLODE ON IGNITION OR IMPACT. CAN CAUSE SEVERE FROSTBITE.
WARNING!
Uninterrupted use of high concentrations of oxygen over long duration,
without monitoring its effect on oxygen content of arterial blood, may
be harmful. Use only with pressure reducing equipment and apparatus
designed for oxygen. Do not attempt to use on patients who have stopped
breathing, unless used in conjunction with resuscitative equipment.
Keep oil, grease, and combustibles away. Use only with equipment
cleaned for oxygen service. Store and use with adequate ventilation. Do
not get liquid in eyes, on skin or clothing. For liquid withdrawal,
wear face shield and gloves. Do not drop. Use hand truck for container
movement. Avoid spills. Do not walk on or roll equipment over spills.
Close valve after each use and when empty. Use in accordance with
Material Safety Data Sheet.
Part #DB-USP
Printed by ratermann MFG inc.